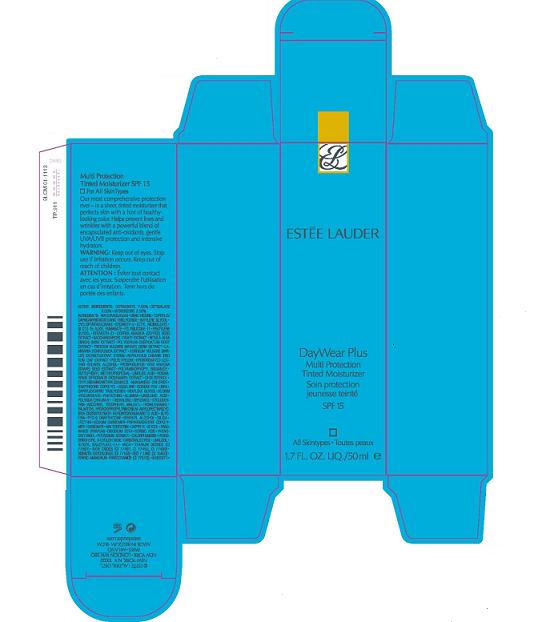 DRUG LABEL: DAYWEAR PLUS MULTI PROTECTION TINTED MOISTURIZER
NDC: 11559-754 | Form: CREAM
Manufacturer: ESTEE LAUDER INC
Category: otc | Type: HUMAN OTC DRUG LABEL
Date: 20100412

ACTIVE INGREDIENTS: OCTINOXATE 7.5 mL/100 mL; OCTISALATE 5.0 mL/100 mL; AVOBENZONE 2.0 mL/100 mL

ACTIVE INGREDIENT

ACTIVE INGREDIENTS: OCTINOXATE 7.50% [] OCTISALATE 5.00% [] AVOBENZONE 2.00%

WARNINGS

WARNING: KEEP OUT OF EYES. STOP USE IF IRRITATION OCCURS. KEEP OUT OF REACH OF CHILDREN.

PACKAGE LABEL

PRINCIPAL DISPLAY PANEL

DAY WEAR PLUS

MULTI PROTECTION

TINTED MOISTURIZER

SPF 15

All Skintypes

1.7 FL OZ LIQ/ 50 ML

ESTEE LAUDER DIST.

NEW YORK, NY 10022

9LCM